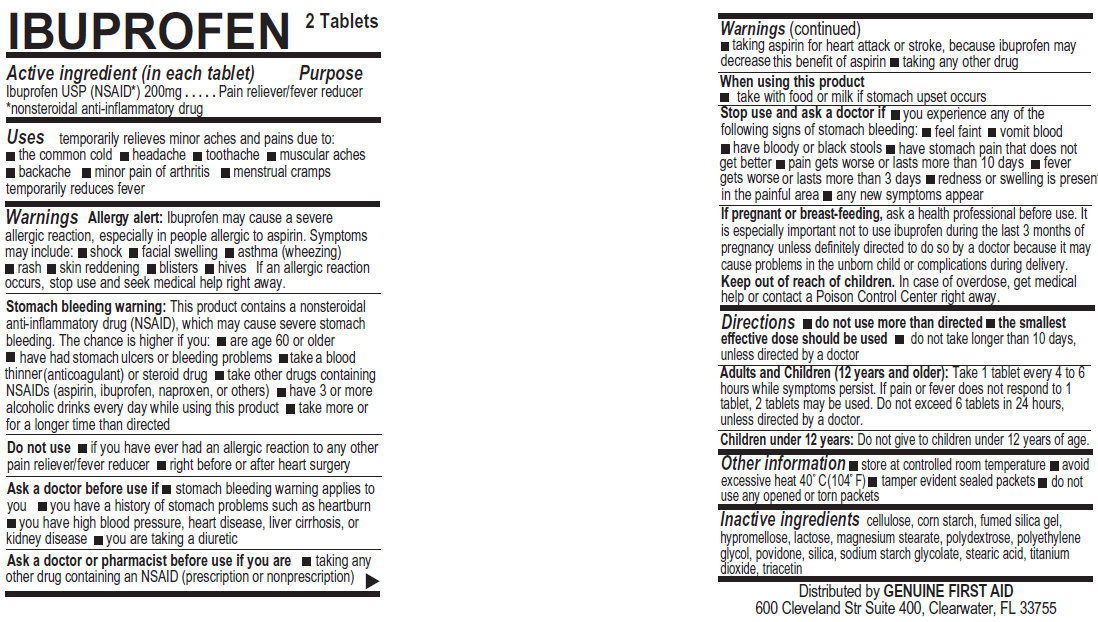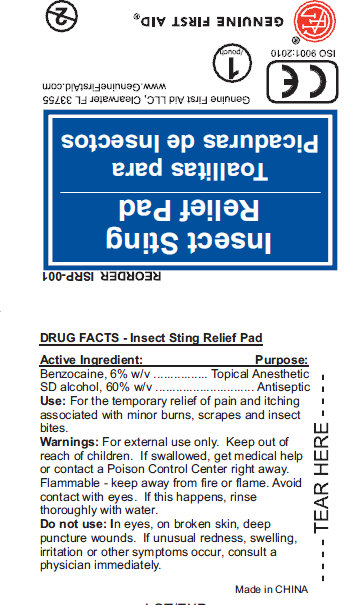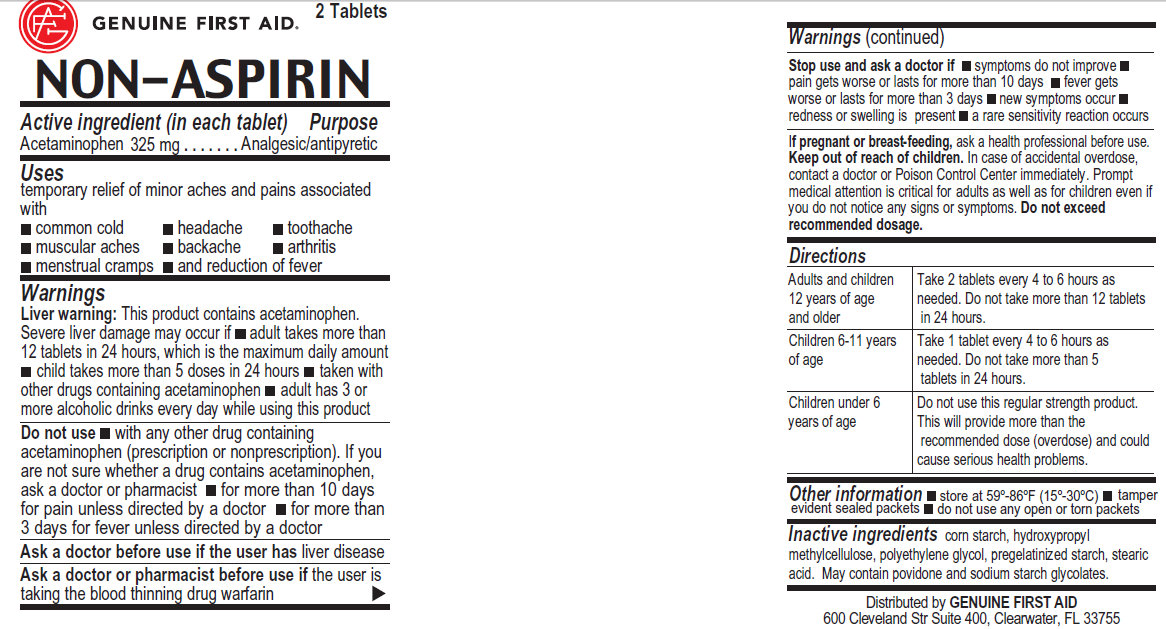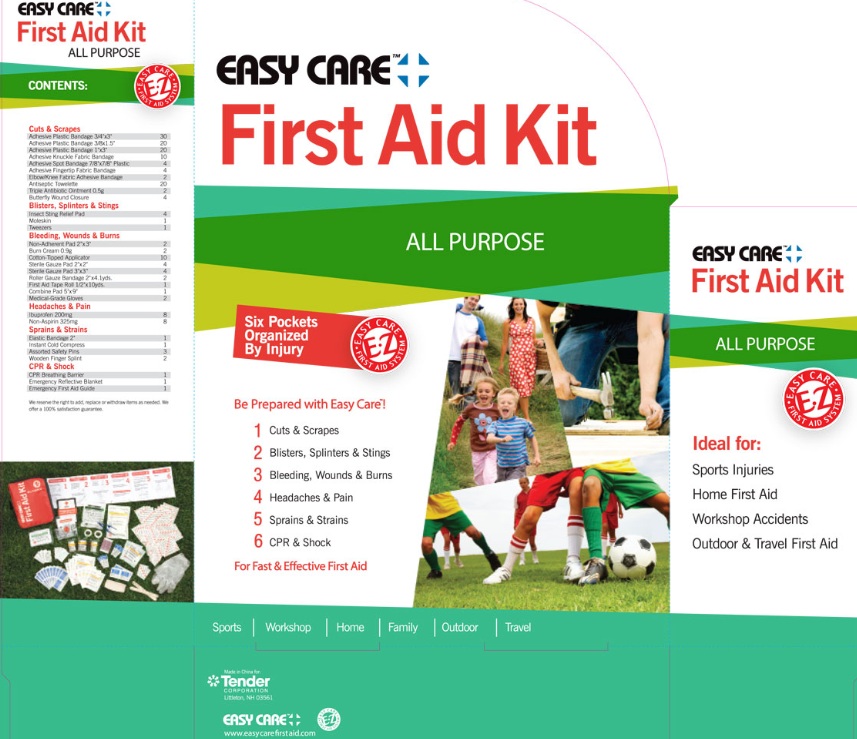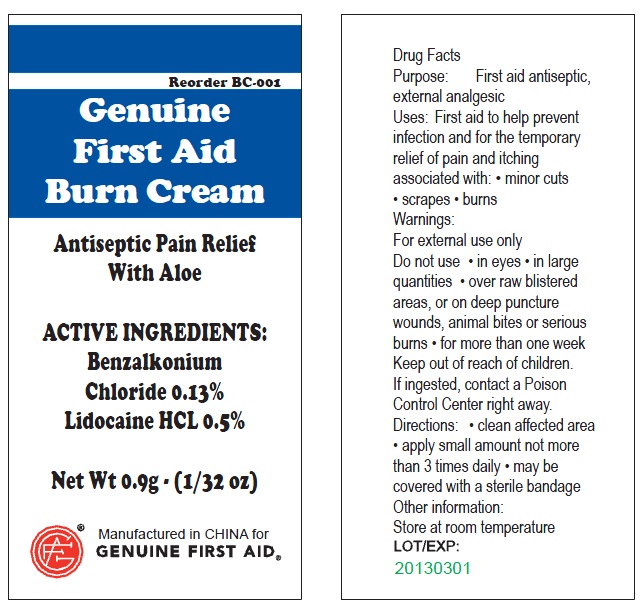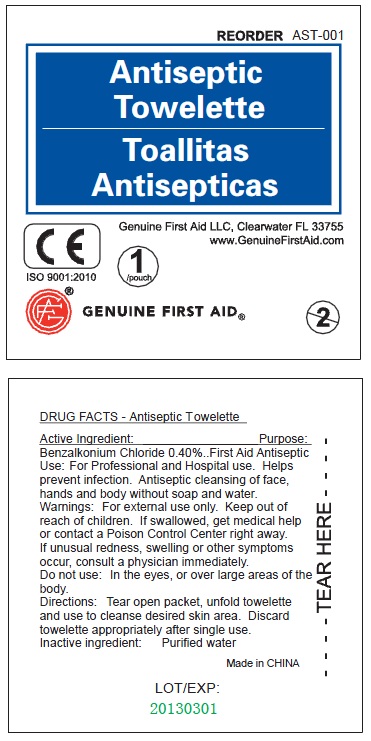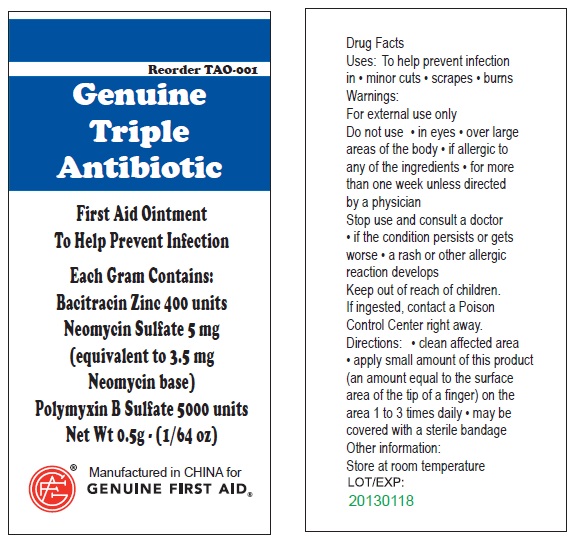 DRUG LABEL: Easy Care First Aid - All Purpose
NDC: 44224-1999 | Form: KIT | Route: TOPICAL
Manufacturer: Tender Corp dba Adventure Medical Kits
Category: otc | Type: HUMAN OTC DRUG LABEL
Date: 20110415

ACTIVE INGREDIENTS: BENZALKONIUM CHLORIDE 0.4 mL/100 mL; BENZOCAINE 6 mL/100 mL; ALCOHOL 60 mL/100 mL; BACITRACIN ZINC 400 [iU]/1 g; NEOMYCIN SULFATE 5 mg/1 g; POLYMYXIN B SULFATE 5000 [iU]/1 g; ACETAMINOPHEN 325 mg/1 1; IBUPROFEN 200 mg/1 1; BENZALKONIUM CHLORIDE 0.13 g/100 g; LIDOCAINE 0.5 g/100 g
INACTIVE INGREDIENTS: WATER; WATER; WATER; STARCH, CORN; POLYETHYLENE GLYCOL; STEARIC ACID; POVIDONE; POWDERED CELLULOSE; STARCH, CORN; HYPROMELLOSES
; LACTOSE; MAGNESIUM STEARATE; POLYDEXTROSE; POLYETHYLENE GLYCOL; POVIDONE; SILICON DIOXIDE; STEARIC ACID; TITANIUM DIOXIDE; TRIACETIN; ALOE VERA LEAF; CETYL ALCOHOL; DIAZOLIDINYL UREA; EDETATE DISODIUM; GLYCERIN; GLYCERYL MONOSTEARATE; METHYLPARABEN; MINERAL OIL ; POLYETHYLENE GLYCOL; PROPYLENE GLYCOL; PROPYLPARABEN; WATER; STEARIC ACID

Easy Care First Aid Kit Sports and Travel

Active Ingredient

Benzalkonium Chloride 0.40%

Purpose

Antiseptic

Use

For Professional and Hospital use. Helps prevent infection. Antiseptic cleansing of face, hands and body without soap and water.

Warnings

Warning: For external use only.

Keep out of reach of children: If swallowed, get medical help or contact a Poison Control Center right away.

Stop use if unusual redness, swelling or other symptoms occur. Consult a physician immediately.

Do not use in the eyes or over large areas of the body.

Directions

Tear open packet, unfold towelette and use to cleanse desired skin area. Discard towelette appropriately after single use.

Inactive Ingredients

Inactive Ingredient: Purified water

LOT/EXP: Made in CHINA

20130301

PACKAGE LABEL

Antiseptic Towelette

Genuine First Aid LLC, Clearwater FL 33755

www.GenuineFirstAid.com

1/pouch

GENUINE FIRST AID

Active Ingredient: Purpose:

Benzocaine, 6% w/v.................. Topical Anesthetic

SD alcohol, 60% w/v.................. Antiseptic

PURPOSE

Use: For the temporary relief of pain and itching associated with minor burns, scrapes and insect bites.

Warnings: For external use only.

Avoid contact with eyes. If this happens, rinse thoroughly with water.

Keep out of reach of children. If swallowed, get medical help or contact a Poison Control Center right away.

STORAGE AND HANDLING

Flammable - keep away from fire or flame.

Do not use: In eyes, on broken skin, deep puncture wounds. If unusual redness, swelling, irritation or other symptoms occur, consult a physician immediately.

DESCRIPTION

Made in CHINA

LOT/EXP:

PACKAGE LABEL

Insect Sting Relief Pad

Genuine First Aid LLC, Clearwater FL 33755
www.GenuineFirstAid.com
1/pouch
GENUINE FIRST AID

Active Ingredients

Active Ingredient: .........Bacitracin Zinc 400 units

Neomycin Sulfate 5mg (equivalent to 3.5 mg Neomycin base)

Polymyxin B Sulfate 5000 units

Purpose

Triple Antibiotic

INDICATIONS AND USAGE

Uses: To help prevent infection in:
minor cuts; scrapes; burns

Warnings

For external use only.

Do not use: in eyes; over large areas of the body;

If allergic to any of the ingredients; for more than one week unless directed by a physician.

Stop use and consult a doctor:

if the condition persists or gets worse; a rash or other allergic reaction develops

Keep out of reach of children.

If ingested, contact a Poison

Control Center right away.

Directions

Directions: clean affected area; apply small amount of this product (an amount equal to the surface area of the tip of a finger) on the area 1 to 3 times daily; may be covered with a sterile bandage

Other information:

Store at room temperature.

Inactive Ingredient

water

PACKAGE LABEL

Genuine Triple Antibiotic

First Aid Ointment

To Help Prevent Infection

Each Gram Contains:

Bacitracin Zinc 400 units

Neomycin Sulfate 5 mg

(equivalent to 3.5 mg

Neomycin base)

Polymyxin B Sulfate 5000 units

Net Wt. 0.5g ; (1/64 oz)

Manufactured in CHINA for

GENUINE FIRST AID.

Triple Antibiotic Ointment 10pcs

Net wt. 0.9g (1/32oz)

100
Triple Antibiotic

Active Ingredient (in each tablet) Purpose

Acetaminophen 325 mg ............. Analgesic/antipyretic

Uses

temporary relief of minor aches and pains associated with:

common cold; headache; toothache; muscular aches; backache; arthritis; menstrual cramps; and reduction of fever

Warnings:

Liver warning: This product contains acetaminophen.

Severe liver damage may occur if: adult takes more than 12 tablets in 24 hours, which is the maximum daily amount; child takes more than 5 doses in 24 hours; taken with other drugs containing acetaminophen; adult has 3 or more alcoholic drinks every day while using this product

Do not use: with any other drug containing acetaminophen (prescription or nonprescription). If you are not sure whether a drug contains acetaminophen, ask a doctor or pharmacist; for more than 10 days for pain unless directed by a doctor; for more than 3 days for fever unless directed by a doctor

Ask a doctor before use if the user has liver disease

Ask a doctor or pharmacist before use if the user is taking the blood thinning drug warfarin

Stop use and ask a doctor if: symptoms do not improve; pain gets worse or lasts for more than 10 days; fever gets worse or lasts for more than 3 days; new symptoms occur; redness or swelling is present; a rare sensitivity reaction occurs

PREGNANCY OR BREAST FEEDING

If pregnant or breast-feeding, ask a health professional before use.

Keep out of reach of children. In case of accidental overdose, contact a doctor or Poison Control Center immediately. Prompt
medical attention is critical for adults as well as for children even if
you do not notice any signs or symptoms. Do not exceed recommended dosage

Directions

Adults and Children Take 2 tablets every 4 to 6 hours as

12 years of age needed. Do not take more than 12 tablets

or older in 24 hours.

Children 6-11 years Take 1 tablet every 4 to 6 hours as

of age needed. Do not take more than 5

tablets in 24 hours.

Children under 6 Do not use this regular strength product.

years of age This will provide more than the

recommended dose (overdose) and could

cause serious health problems.

STORAGE AND HANDLING

Store at 59-86 degree F (15-30 degree C)

GENERAL PRECAUTIONS

tamper evident sealed packets; do not use any open or torn packets

DESCRIPTION

Distributed by GENUINE FIRST AID
600 Cleveland Str Suite 400, Clearwater, FL 33755

PACKAGE LABEL

GENUINE FIRST AID 2 Tablets

NON-ASPIRIN

Active ingredient (in each tablet) Purpose

Ibuprofen USP (NSAID*) 200mg . . . . . . . . . . . .Pain reliever/fever reducer

*nonsteroidal anti-inflammatory drug

PURPOSE

Uses temporarily relieves minor aches and pains due to:
the common cold
headache
toothache
muscular aches
backache
minor pain of arthritis
menstrual cramps temporarily reduces fever

Warnings

Allergy alert: Ibuprofen may cause a severe allergic reaction, especially in people allergic to aspirin. Symptoms may include: shock, facial swelling, asthma (wheezing) rash, skin reddening, blisters, hives If an allergic reaction occurs, stop use and seek medical help right away.

Stomach bleeding warning: This product contains a nonsteroidal anti-inflammatory drug (NSAID), which may cause severe stomach
bleeding. The chance is higher if you: are age 60 or older, have had stomach ulcers or bleeding problems, take a blood thinner (anticoagulant) or steroid drug, take other drugs containing NSAIDs (aspirin, ibuprofen, naproxen, or others), have 3 or more alcoholic drinks every day while using this product, take more or for a longer time than directed

Do not use if you have ever had an allergic reaction to any other pain reliever/fever reducer, right before or after heart surgery.

Ask a doctor before use if stomach bleeding warning applies to you; you have a history of stomach problems such as heartburn; you have a high blood pressure, heart disease, liver cirrhosis, or kidney disease; you are taking a diuretic

Ask a doctor before use if you are:
taking any other drug containing NSAID (prescription or nonprescription); taking aspirin for heart attack or stroke, because Ibuprofen may decrease this benefit of aspirin; taking any other drug

When using this product:
take with food or milk if stomach upset occurs

Stop use and ask a doctor If:
you experience any of the following signs of stomach bleeding; feel faint; vomit blood; have bloody or black stools; have stomach pain that does get better; pain gets worse or lasts more than 10 days; fever gets worse or lasts more than 3 days; redness or swelling is present in the painful area; any new symptoms appear

PREGNANCY OR BREAST FEEDING

If pregnant or breast-feeding, ask a health professional before use. It is especially important not to use ibuprofen during the last 3 months of pregnancy unless definitely directed to do so by a doctor because it may cause problems in the unborn child or complications during delivery.

Keep out of reach of children. In case of overdose, get medical help or contact a Poison Control Center right away.

Directions:
do not use more than directed; the smallest effective dose should be used; do not take longer than 10 days, unless directed by a doctor.
Adults and Children (12 years and older): Take 1 tablet every 4 to 6 hours while symptoms persist. If pain or fever does not respond to 1 tablet, 2 tablets may be used. Do not exceed 6 tablets in 24 hours, unless directed by a doctor.
Children under 12 years: Do not give to children under 12 years of age.

Other information: Store at controlled room temperature; avoid excessive heat 40 degree Celsius (104 degree Fahrenheit); tamper evident sealed packets; do not use any opened or torn packets

INACTIVE INGREDIENT

Inactive ingredients: cellulose, corn starch, fumed silica gel, hypromellose, lactose, magnesium stearate, polydextrose, polyethylene glycol, povidone, silica, sodium starch glycolate, stearic acid, titanium dioxide, triacetin.

DESCRIPTION

Distributed by GENUINE FIRST AID
600 Cleveland Str Suite 400, Clearwater, FL 33755

PACKAGE LABEL

IBUPROFEN 2 Tablets

Active Ingredients

Benzalkonium Chloride 0.13%
Lidocaine HCL 0.5%

Purpose

Purpose: First aid antiseptic, external analgesic

Uses

First aid to help prevent infection and for the temporary relief of pain and itching associated with:

Minor Cuts

Scrapes

Burns

Warnings

For external use only

Do not use: In eyes, in large quantities, over raw blistered areas, or on deep puncture wounds, animal bites or serious burns, for more than one week
Do not use:
in the eyes or apply over large areas of the body.
longer than 1 week unless directed by a doctor.
in large quantities, particularly over raw surfaces or blistered areas.
Ask a doctor before use if you have deep puncture wounds, animal bites or serious burns.
When using this product, avoid contact with the eyes.

Stop use and ask a doctor if
condition worsens
symptoms persist for more than 7 days
condition clears up and occurs again within a few days

Keep out of reach of Children.
If ingested, contact a Poison Control Center right away.

Directions

Adults and children 2 years of age and older

clean affected area.

apply a small amount of this product on the area 1 to 3 times daily.

may be covered with a sterile bandage

children under 2 years of age: consult a doctor

Other Information:
Store at room temperature (do not freeze).

Taper evident sealed packets.

Do not use packet if opened or torn.

Inactive Ingredients

Aloe vera, cetyl alcohol, diazolidinyl urea, edetate disodium, glycerin, glyceryl monostearate, methylparaben, mineral oil, polyethylene glycol, propylene glycol, propylparaben, purified water, stearic acid, irolamine

DESCRIPTION

LOT/EXP: Made in CHINA
20130301

GFA Production Xiamen Co., Ltd
No. 20 Huli Industrial Park, Meixi Road, Tong'an, Xiamen, Fujian, China 361100
Tel: 86-592-7269515 Fax: 86-592-7269528 Http: //www.gfaproduction.com

PACKAGE LABEL

Genuine First Aid Burn Cream
Antiseptic Pain Relief With Aloe
Net Wt 0.9g (1/32 oz)
Manufactured in CHINA for
Genuine First Aid.